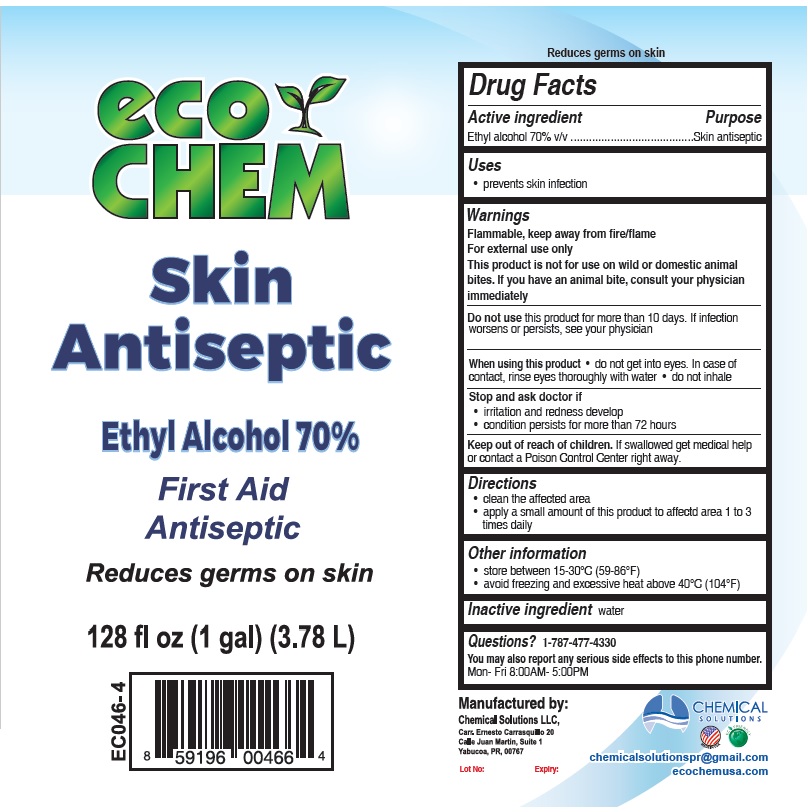 DRUG LABEL: Eco Chem Skin Antiseptic
NDC: 75650-002 | Form: LIQUID
Manufacturer: Chemical Solutions, LLC
Category: otc | Type: HUMAN OTC DRUG LABEL
Date: 20200622

ACTIVE INGREDIENTS: ALCOHOL 70 mL/100 mL
INACTIVE INGREDIENTS: WATER

eco CHEM Skin Antiseptic

Active ingredient

Ethyl alcohol 70% v/v

Purpose

Skin antiseptic

Uses

• prevents skin infection

Warnings

Flammable, keep away from fire/flame
For external use only
This product is not for use on wild or domestic animal bites. If you have an animal bite, consult your physician immediately

Do not use this product for more than 10 days. If infection worsens or persists, see your physician

When using this product • do not get into eyes. In case of contact, rinse eyes thoroughly with water • do not inhale

Stop and ask doctor if

• irritation and redness develop
• condition persists for more than 72 hours

Keep out of reach of children.

If swallowed get medical help or contact a Poison Control Center right away.

Directions

• clean the affected area
• apply a small amount of this product to affected area 1 to 3 times daily

Other information

• store between 15-30° C (59-86° F)
• avoid freezing and excessive heat above 40° C (104° F)

Inactive ingredient

water

Questions?

1-787-477-4330
You may also report any serious side effects to this phone number.
Mon- Fri 8:00AM- 5:00PM

Ethyl Alcohol 70%

First Aid Antiseptic

Reduces germs on skin

Manufactured by:

Chemical Solutions LLC,

Carr. Ernesto Carrasquillo 20

Calle Juan Martin, Suite 1

Yabucoa, PR, 00767

Lot No:

Expiry:

chemicalsolutionspr@gmail.com
ecochemusa.com